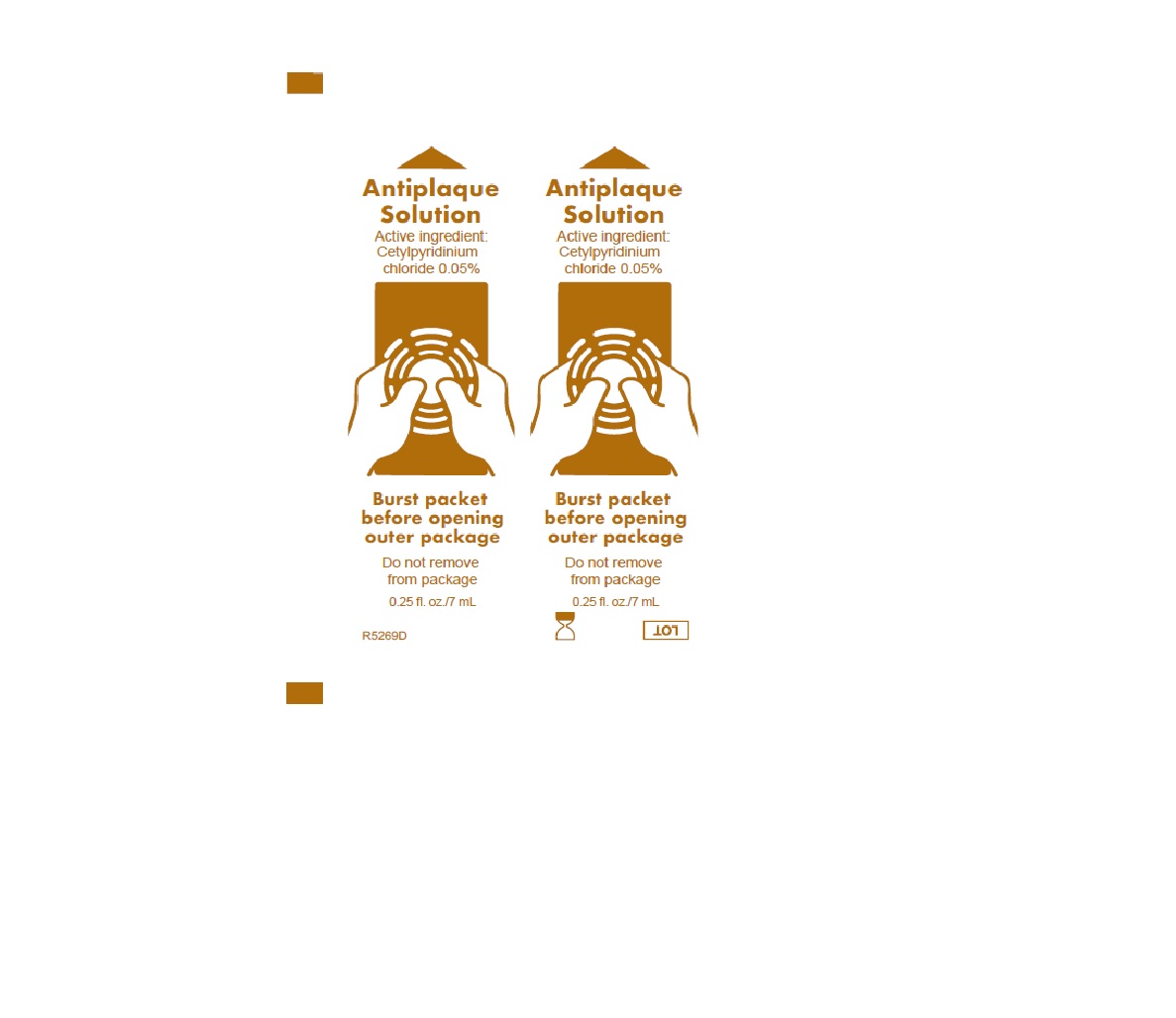 DRUG LABEL: Antiplaque solution
NDC: 53462-275 | Form: MOUTHWASH
Manufacturer: Sage Products LLC
Category: otc | Type: HUMAN OTC DRUG LABEL
Date: 20251208

ACTIVE INGREDIENTS: CETYLPYRIDINIUM CHLORIDE 0.5 mg/1 mL
INACTIVE INGREDIENTS: WATER; SORBITOL; PEPPERMINT; POTASSIUM SORBATE; FD&C BLUE NO. 1; POLYSORBATE 80; POLYSORBATE 20; CITRIC ACID MONOHYDRATE

Antiplaque Solution

Active ingredient

ANTIPLAQUE:
Cetylpyridinium chloride .05%

Purpose

Antigingivitis/antiplaque

Uses

Aids in the removal and prevention of plaque that leads to gingivitis.

Warnings

Stop use and ask a dentist if:

- Gingivitis, bleeding or redness persists for more than 2 weeks.
- You have painful or swollen gums, pus from the gum line, loose teeth or increasing spacing between the teeth. These may be signs or symptoms of periodontitis, a serious form of gum disease.

Keep out of reach of children under 6 year of age. If more than used for brushing is accidentally swallowed, get medical help or contact a Poison Control Center right away.

Directions

- Before opening, turn package over, burst solution packet with thumbs.
- Peel lid to open.
- Remove Mouth Moisturizer and Applicator Swab.
- Attach Toothbrush to suction line.
- Clean teeth and oral cavity for approximately one minute.
- To suction, place thumb over port.
- To clear tubing, rinse with sterile saline or appropriate solution.
- Discard Toothbrush. Reattach Covered Yankauer to suction line.
- Place Mouth Moisturizer on Applicator Swab.
- Apply as needed to lips and inside mouth.

- Adults and children 12 years of age and older: use two times daily or as directed by a dentist. Do not swallow the solution.
- Children ages 6 to 12 years: supervise use.
- Children under 6 years of age: do not use.
- Use a bite block when performing oral care on patients with altered levels of consciousness or those who cannot comprehend commands.
- Ensure foam is intact after use. If not, remove any particles from oral cavity.

Inactive ingredients

Water, sorbitol, peppermint flavor, potassium sorbate, polysorbate 80, polysorbate 20, citric acid, FD&C Blue #1

Questions

Call toll-free 800-323-2220